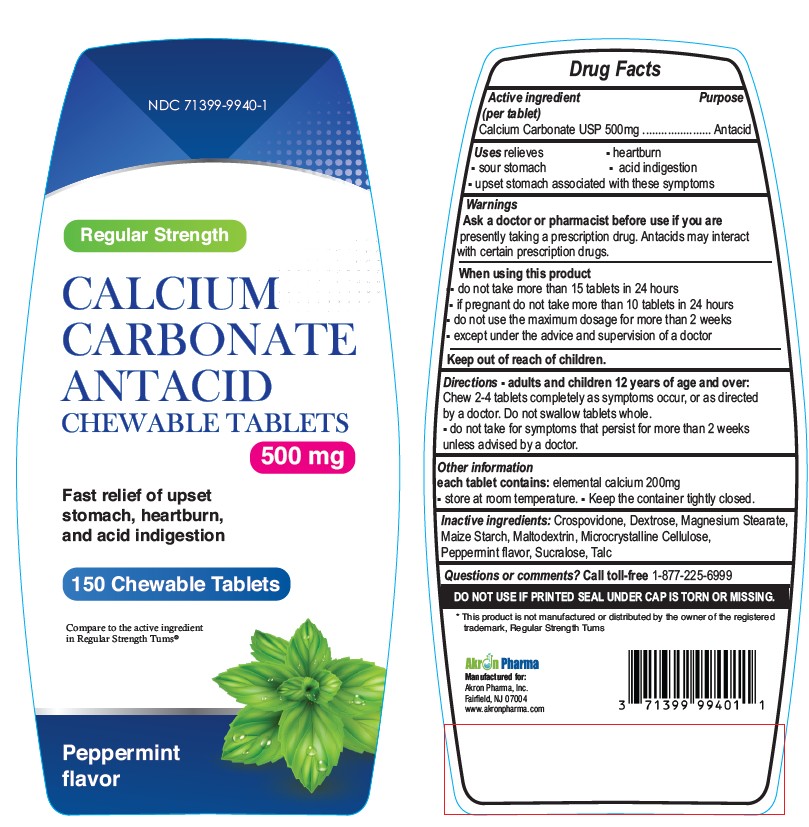 DRUG LABEL: REGULAR STRENGTH ANTACID
NDC: 71399-9940 | Form: TABLET, CHEWABLE
Manufacturer: AKRON PHARMA INC
Category: otc | Type: HUMAN OTC DRUG LABEL
Date: 20250926

ACTIVE INGREDIENTS: CALCIUM CARBONATE 500 mg/1 1
INACTIVE INGREDIENTS: DEXTROSE, UNSPECIFIED FORM; MAGNESIUM STEARATE; MALTODEXTRIN; STARCH, CORN; CELLULOSE, MICROCRYSTALLINE; SUCRALOSE; TALC

Antacid Regular Strength Peppermint 150 Chewable Tablets

Active ingredient (Per tablet)

Calcium Carbonate USP 500mg

Purpose

Antacid

Uses

relieves:

- heartburn
- acid indigestion
- sour stomach
- upset stomach associated with these symptoms

Warnings

Ask a doctor or pharmacist before use if you arepresently taking a prescription drug. Antacids may interact with certain prescription drugs.

When using this product

- do not take more than 15 tablets in 24 hours
- if pregnant do not take more than 10 tablets in 24 hours
- do not use the maximum dosage for more than 2 weeks except under the advice and supervision of a doctor

Keep out of Reach of Children

Directions

- adults and children 12 years of age and over:Chew 2-4 tablets as symptoms occur, or as directed by a doctor.
- do not take for symptoms that persist for more than 2 weeks unless advised by a doctor

Other Information

- each tablet contains : elemental calcium 200mg
- Store at room temperature. Keep the container tightly closed.

Inactive ingredients

Crospovidone, Dextrose, Magnesium Stearate,Maize Starch, Maltodextrin, Microcrystalline Cellulose, Peppermint flavor, Sucralose, Talc

Question or comments?

Call Toll Free 1-877-225-6999

Safety sealed: Do not use if printed seal under cap is torn or missing

* This product is not manufactured or distributed by the owner of the registered trademark, Regular Strength Tums

Manufactured for:
Akron Pharma, Inc.
Fairfield, NJ 07004
www.akronpharma.com